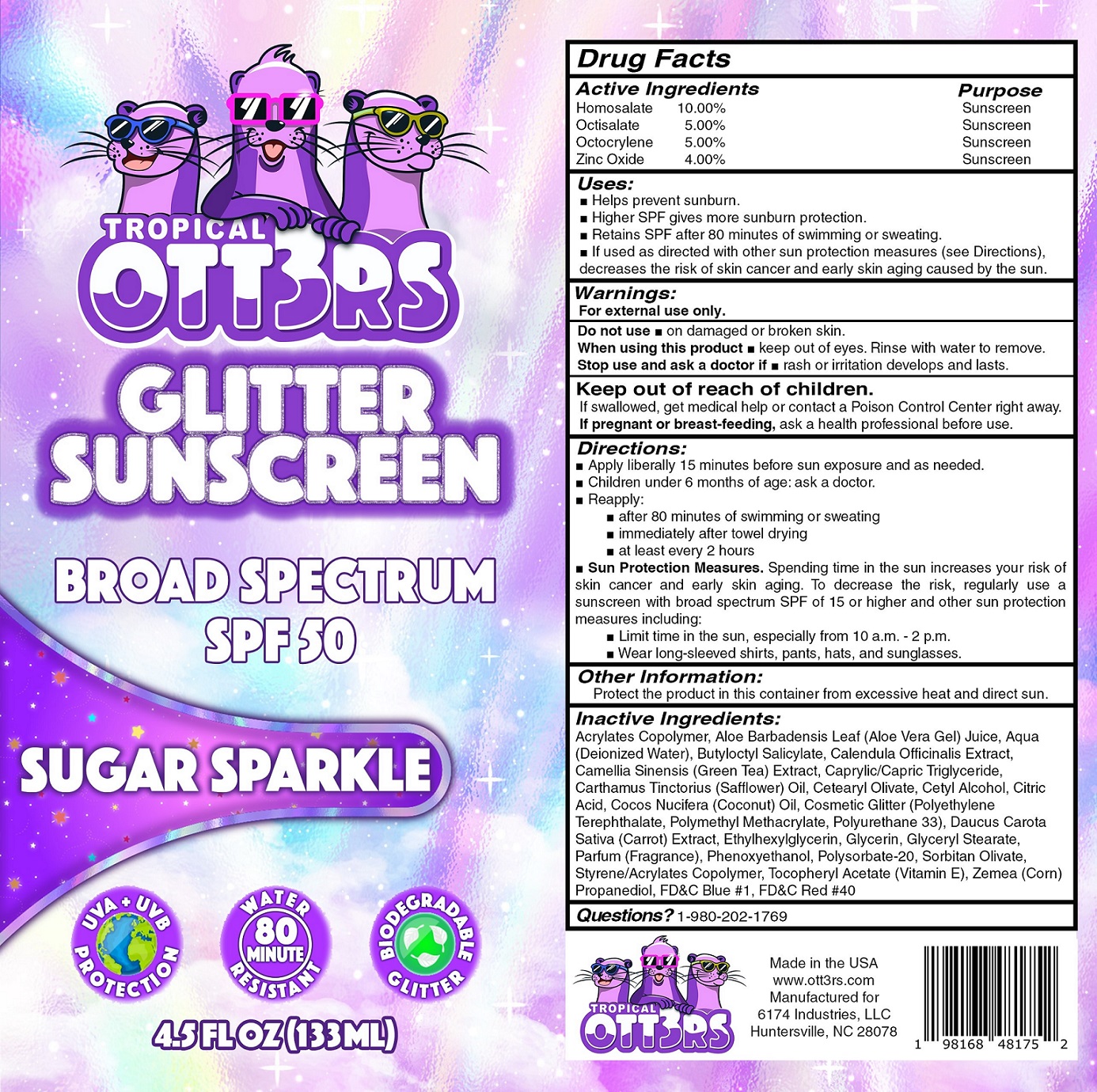 DRUG LABEL: TROPICAL OTTERS Glitter Sunscreen SPF-50 - Sugar Sparkle
NDC: 84164-460 | Form: CREAM
Manufacturer: 6174 INDUSTRIES, LLC
Category: otc | Type: HUMAN OTC DRUG LABEL
Date: 20240306

ACTIVE INGREDIENTS: HOMOSALATE 100 mg/1 mL; OCTISALATE 50 mg/1 mL; OCTOCRYLENE 50 mg/1 mL; ZINC OXIDE 40 mg/1 mL
INACTIVE INGREDIENTS: ALOE VERA LEAF; WATER; BUTYLOCTYL SALICYLATE; CALENDULA OFFICINALIS FLOWER; GREEN TEA LEAF; MEDIUM-CHAIN TRIGLYCERIDES; SAFFLOWER; CETEARYL OLIVATE; CETYL ALCOHOL; CITRIC ACID MONOHYDRATE; COCONUT OIL; CARROT; ETHYLHEXYLGLYCERIN; GLYCERIN; GLYCERYL MONOSTEARATE; PHENOXYETHANOL; POLYSORBATE 20; SORBITAN OLIVATE; .ALPHA.-TOCOPHEROL ACETATE; CORN; FD&C BLUE NO. 1; FD&C RED NO. 40

TROPICAL OTTERS Glitter Sunscreen SPF-50 - Sugar Sparkle

Active Ingredients

Homosalate 10.00%
Octisalate 5.00%
Octocrylene 5.00%
Zinc Oxide 4.00%

Purpose

Sunscreen

Uses:

- Helps prevent sunburn.
- Higher SPF gives more sunburn protection.
- Retains SPF after 80 minutes of swimming or sweating.
- If used as directed with other sun protection measures (see Directions), decreases the risk of skin cancer and early skin aging caused by the sun.

Warnings:

For external use only.

Do not use

- on damaged or broken skin.

When using this product

- keep out of eyes. Rinse with water to remove.

Stop use and ask a doctor if

- rash or irritation develops and lasts.

Keep out of reach of children.

If swallowed, get medical help or contact a Poison Control Center right away.

If pregnant or breast-feeding,

ask a health professional before use.

Directions

- Apply liberally15 minutes before sun exposure and as needed.
- Children under 6 months of age: ask a doctor.
- Reapply:
- after 80 minutes of swimming or sweating
- immediately after towel drying.
- at least every 2 hours.
- Sun Protection Measures.Spending time in the sun increases your risk of skin cancer and early skin aging. To decrease this risk, regularly use a sunscreen with broad spectrum SPF of 15 or higher and other sun protection measures including:
- Limit time in the sun, especially from 10 a.m.-2 p.m.
- Wear long-sleeved shirts, pants, hats, and sunglasses.

Other Information:

Protect the product in this container from excessive heat and direct sun.

Inactive Ingredients:

Acrylates Copolymer, Aloe Barbadensis Leaf (Aloe Vera Gel) Juice, Aqua (Deionized Water), Butyloctyl Salicylate, Calendula Officinalis Extract, Camellia sinensis (Green Tea) Extract, Caprylic/Capric Triglyceride, Carthamus Tinctorius (Safflower) Oil, Cetearyl Olivate, Cetyl Alcohol, Citric Acid, Cocos Nucifera (Coconut) Oil, Cosmetic Glitter (Polyethylene Terephthalate, Polymethyl Methacrylate, Polyurethane 33), Daucus Carota Sativa (Carrot) Extract, Ethylhexylglycerin, Glycerin, Glyceryl Stearate, Parfum (Fragrance), Phenoxyethanol, Polysorbate-20, Sorbitan Olivate, Styrene/Acrylates Copolymer, Tocopheryl Acetate (Vitamin E), Zemea (Corn) Propanediol, FD&C Blue #1, FD&C Red #40

Questions?

1-980-202-1769